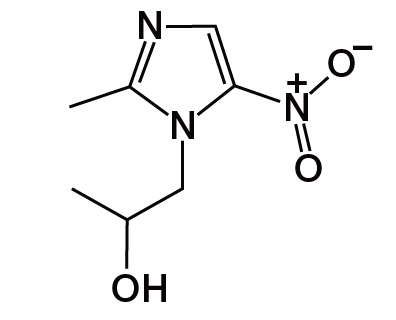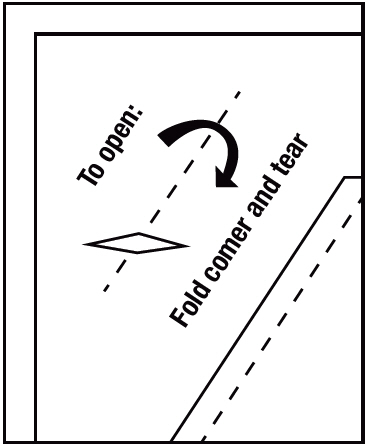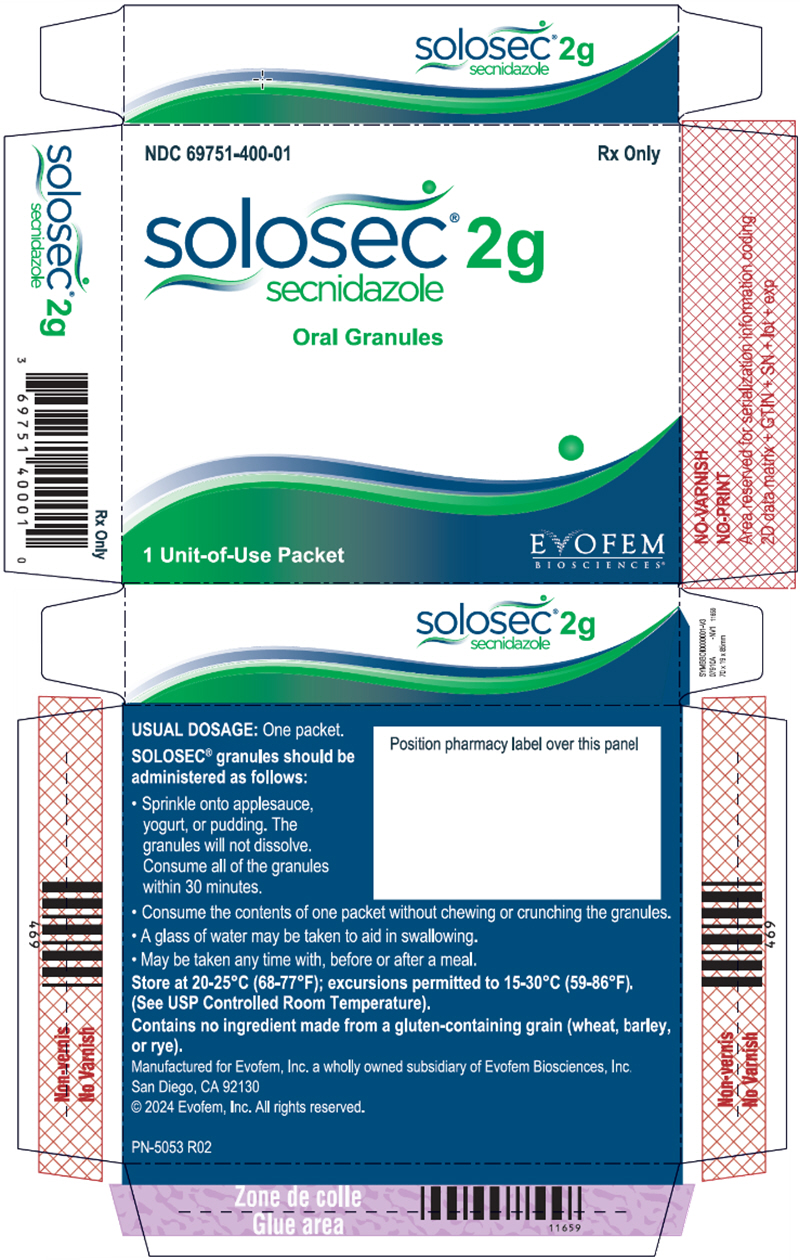 DRUG LABEL: Solosec
NDC: 69751-400 | Form: GRANULE
Manufacturer: Evofem Inc.
Category: prescription | Type: HUMAN PRESCRIPTION DRUG LABEL
Date: 20250219

ACTIVE INGREDIENTS: secnidazole 2 g/4.8 g
INACTIVE INGREDIENTS: ETHYL ACRYLATE AND METHYL METHACRYLATE COPOLYMER (2:1; 750000 MW); POVIDONE, UNSPECIFIED; POLYETHYLENE GLYCOL 4000; SUCROSE; talc

HIGHLIGHTS OF PRESCRIBING INFORMATION

These highlights do not include all the information needed to use SOLOSEC® safely and effectively. See full prescribing information for SOLOSEC.
SOLOSEC® (secnidazole) oral granules
Initial U.S. Approval: 2017

1 INDICATIONS AND USAGE

SOLOSEC® is a nitroimidazole antimicrobial indicated for:

- Treatment of bacterial vaginosis in female patients 12 years of age and older. (1.1)
- Treatment of trichomoniasis in patients 12 years of age and older. (1.2)

To reduce the development of drug-resistant bacteria and maintain the effectiveness of SOLOSEC and other antibacterial drugs, SOLOSEC should be used only to treat or prevent infections that are proven or strongly suspected to be caused by bacteria. (1.3)

2 DOSAGE AND ADMINISTRATION

- Bacterial Vaginosis (female patients 12 years of age and older): Administer a single 2-gram packet of granules once orally, without regard to the timing of meals. (2.1)
- Trichomoniasis (patients 12 years of age and older): Administer a single 2-gram packet of granules once orally, without regard to the timing of meals. Treat sexual partners with the same dose and at the same time. (2.2)
- Sprinkle entire contents of packet onto applesauce, yogurt or pudding and consume all of the mixture within 30 minutes without chewing or crunching the granules. A glass of water may be taken after the administration of SOLOSEC to aid in swallowing. (2.3)
- SOLOSEC is not intended to be dissolved in any liquid. (2.3)

3. DOSAGE FORMS AND STRENGTHS

Oral granules: 2 g secnidazole, in a unit-of-use child-resistant foil packet. (3)

4. CONTRAINDICATIONS

- History of hypersensitivity to secnidazole, or other nitroimidazole derivatives. (4)
- Patients with Cockayne syndrome. (4, 6.2)

5 WARNINGS AND PRECAUTIONS

- Vulvovaginal Candidiasis: This may develop with SOLOSEC and require treatment with an antifungal agent. (5.1)
- Potential Risk for Carcinogenicity: Carcinogenicity has been seen in mice and rats treated chronically with nitroimidazole derivatives, which are structurally related to secnidazole. It is unclear if the positive tumor findings in lifetime rodent studies indicate a risk to patients taking a single dose of SOLOSEC to treat bacterial vaginosis. Avoid chronic use. (5.2)

6 ADVERSE REACTIONS

- Bacterial Vaginosis: Most common adverse reactions observed in clinical trials of bacterial vaginosis (incidence ≥ 2%) were vulvovaginal candidiasis, headache, nausea, dysgeusia, vomiting, diarrhea, abdominal pain, and vulvovaginal pruritus. (6.1).
- Trichomoniasis: Most common adverse reaction observed in the clinical trial of trichomoniasis (incidence ≥ 2%) was vulvovaginal candidiasis. (6.1).

To report SUSPECTED ADVERSE REACTIONS, contact Evofem at toll-free-phone 1-833-EVFMBIO (1-833-383-6246) or FDA at 1-800-FDA-1088 or www.fda.gov/medwatch.

8 USE IN SPECIFIC POPULATIONS

Lactation: Breastfeeding is not recommended. Discontinue breastfeeding for 96 hours after administration of SOLOSEC. (8.2)

FULL PRESCRIBING INFORMATION

1 INDICATIONS AND USAGE

1.1 Bacterial Vaginosis

SOLOSEC is indicated for the treatment of bacterial vaginosis in female patients 12 years of age and older [see Use in Specific Populations (8.1) and Clinical Studies (14)].

1.2 Trichomoniasis

SOLOSEC is indicated for the treatment of trichomoniasis caused by Trichomonas vaginalis in patients 12 years of age and older. Because trichomoniasis is a sexually transmitted disease with potentially serious sequelae, treat partners of infected patients simultaneously in order to prevent reinfection [see Dosage and Administration (2.2) and Clinical Studies (14.2)].

1.3 Usage

To reduce the development of drug-resistant bacteria and maintain the effectiveness of SOLOSEC and other antibacterial drugs, SOLOSEC should be used only to treat or prevent infections that are proven or strongly suspected to be caused by susceptible bacteria. When culture and susceptibility information are available, they should be considered in selecting or modifying antibacterial therapy. In the absence of such data, local epidemiology and susceptibility patterns may contribute to the empiric selection of therapy.

2 DOSAGE AND ADMINISTRATION

2.1 Recommended Dosage for Bacterial Vaginosis

The recommended dosage of SOLOSEC for the treatment of bacterial vaginosis in female patients 12 years of age and older is a single 2-gram packet of granules taken once orally, without regard to the timing of meals [see Clinical Pharmacology (12.3)].

2.2 Recommended Dosage for Trichomoniasis

The recommended dosage of SOLOSEC for the treatment of trichomoniasis in patients 12 years of age and older is a single 2-gram packet of granules taken once orally, without regard to the timing of meals [see Clinical Pharmacology (12.3)]. Since trichomoniasis is a sexually transmitted disease, treat sexual partners with the same dose and at the same time [see Indications and Usage (1.2)].

2.3 Instructions for the Preparation and Administration of SOLOSEC

- Open the SOLOSEC packet by folding over the corner (marked by an arrow) and tearing across the top.
- Sprinkle the entire contents of the SOLOSEC packet onto applesauce, yogurt or pudding [see Clinical Pharmacology (12.3)]. The granules will not dissolve. Consume all of the mixture within 30 minutes without chewing or crunching the granules. A glass of water may be taken after the administration of SOLOSEC to aid in swallowing.
- The granules are not intended to be dissolved in any liquid.
- Avoid consumption of alcoholic beverages and preparations containing ethanol or propylene glycol during treatment with SOLOSEC and for at least 2 days after completing therapy [see Adverse Reactions (6.2), Drug Interactions (7.2), and Clinical Pharmacology (12.3)].

3. DOSAGE FORMS AND STRENGTHS

Oral Granules: 2 g, of off-white to slightly yellowish granules with 4.8 g net weight, packed in a unit-of-use child-resistant foil packet.

4. CONTRAINDICATIONS

SOLOSEC is contraindicated:

- In patients who have shown hypersensitivity to secnidazole, or other nitroimidazole derivatives.
- In patients with Cockayne syndrome: Severe irreversible hepatotoxicity/acute liver failure with fatal outcomes have been reported after initiation of metronidazole, another nitroimidazole drug, structurally related to secnidazole, in patients with Cockayne syndrome [see Adverse Reactions (6.2)].

5 WARNINGS AND PRECAUTIONS

5.1 Vulvovaginal Candidiasis

The use of SOLOSEC may result in vulvovaginal candidiasis. In controlled clinical trials of non-pregnant women with bacterial vaginosis, vulvovaginal candidiasis developed in 19/197 (9.6%) of patients who received 2 g SOLOSEC and 4/136 (2.9%) subjects who received placebo. In a controlled clinical trial of non-pregnant female patients with trichomoniasis, vulvovaginal candidiasis developed in 2/74 (2.7%) of patients who received 2 g SOLOSEC and 0/73 (0%) subjects who received placebo [see Adverse Reactions (6.1)]. Symptomatic vulvovaginal candidiasis may require treatment with an antifungal agent.

5.2 Potential Risk for Carcinogenicity

Carcinogenicity has been seen in mice and rats treated chronically with nitroimidazole derivatives which are structurally related to secnidazole. It is unclear if the positive tumor findings in lifetime rodent studies of these nitroimidazoles indicate a risk to patients taking a single dose of SOLOSEC to treat bacterial vaginosis. Avoid chronic use of SOLOSEC [see Nonclinical Toxicology (13.1)]

5.3 Risk of Development of Drug Resistance

Prescribing SOLOSEC in the absence of proven or strongly suspected bacterial infection or a prophylactic indication is unlikely to provide benefit to the patient and increases the risk of the development of drug-resistant bacteria.

6 ADVERSE REACTIONS

The following important adverse reactions are discussed in greater detail in other sections of labeling:

- Vulvovaginal Candidiasis [Warnings and Precautions (5.1)]

6.1 Clinical Trials Experience

Because clinical trials are conducted under widely varying conditions, adverse reaction rates observed in the clinical trials of a drug cannot be directly compared to rates in the clinical trials of another drug and may not reflect the rates observed in practice.

Bacterial Vaginosis

The safety data described below reflect exposure to 629 patients, of whom 558 received a 2 g dose of SOLOSEC. SOLOSEC was evaluated in four clinical trials of female patients diagnosed with bacterial vaginosis: two placebo-controlled trials (Trial 1 n=215, Trial 2 n=189) and two uncontrolled safety trials (Trial 3 n=321, Trial 4 n=40).

Most Common Adverse Reactions in Trials 1 and 2

All patients in Trial 1 and Trial 2 received a single oral dose of study medication or placebo. Trial 1 evaluated a 1 g (this dose is not approved) dose (n=71) and a 2 g dose (n=72) of SOLOSEC in patients aged 18 to 54 years. Trial 2 evaluated a 2 g dose (n=125) in patients aged 18 to 54 years. Patients in the placebo-controlled trials were primarily Black or African American (54%) or Caucasian (41%).

Among 197 patients treated with a single 2 g dose of SOLOSEC in the two placebo-controlled trials, Trial 1 and 2, adverse reactions were reported by approximately 29% of patients. Table 1 displays the most common adverse reactions (≥ 2% in SOLOSEC-treated patients) in these two trials. There were no deaths in the trials.

Table 1: Adverse Reactions Occurring (≥ 2 % SOLOSEC-Treated Patients) in the Pooled Placebo-Controlled Trials 1 and 2 in Adult Women with Bacterial Vaginosis
Adverse Reaction | SOLOSEC N=197 n (%) | Placebo N=136 n (%)
Vulvovaginal candidiasis | 19 (9.6) | 4 (2.9)
Headache | 7 (3.6) | 2 (1.5)
Nausea | 7 (3.6) | 1 (0.7)
Diarrhea | 5 (2.5) | 1 (0.7)
Abdominal pain | 4 (2.0) | 2 (1.5)
Vulvovaginal pruritus | 4 (2.0) | 2 (1.5)

Most Common Adverse Reactions in Trial 3

Among the 321 patients in an uncontrolled trial, Trial 3, adverse reactions were reported in 30% of patients. Vulvovaginal candidiasis (8.4%), nausea (5.3%), vomiting (2.5%) and dysgeusia (3.4%) were the most common adverse reactions reported in this trial. Two SOLOSEC-treated patients in Trial 3 discontinued due to vulvovaginal candidiasis.

Most Common Adverse Reactions in Trial 4

In Trial 4, the safety of SOLOSEC was evaluated in a multicenter, uncontrolled, open-label study evaluating the safety and tolerability of SOLOSEC in 40 pediatric patients between the ages of 12 and less than 18 years old all of whom were treated with a 2 g single dose of SOLOSEC. Most patients in this study were either White (60%) or Black/African-American (38%).The overall safety findings of a SOLOSEC 2 g dose in patients aged 12 to 17 years are consistent with findings in adult patients aged 18 to 65 years old. There were no deaths, severe adverse reactions, or discontinuations due to adverse reactions. Adverse reactions occurring in at least one SOLOSEC-treated pediatric patient included: nausea and abdominal pain.

Trichomoniasis

The safety of SOLOSEC was evaluated in 147 female patients with trichomoniasis who participated in Trial 5, a placebo controlled, double blind trial, of whom 143 (97.3%) patients completed the 'Test of Cure' (TOC) visit. In this trial, 74 patients received a single 2-gram oral dose of SOLOSEC, and 73 patients received placebo. The mean age of the patients in this study was 37.7 years, with a range of 15 to 65 years. Most of the patients were Black or African American (134/147; 91.2%). In the primary phase of Trial 5, i.e., baseline to TOC visit, one SOLOSEC-treated patient was discontinued from the study due to nausea and productive cough.

Most Common Adverse Reactions

A total of 11 patients (14.9%) who received SOLOSEC and 16 patients (21.9%) in the placebo group reported adverse reactions, respectively. Vulvovaginal candidiasis was reported in 2 patients (2.7%) in the SOLOSEC-treated group and in none of the patients in the placebo group.

6.2 Postmarketing Experience

The following adverse reactions have been reported during use of SOLOSEC and other 2 g formulations of secnidazole outside of the United States. Because these reactions are reported voluntarily from a population of uncertain size, it is not always possible to reliably estimate their frequency or establish a causal relationship to drug exposure.

Adverse Reactions with SOLOSEC

Nervous System Disorders: Dysgeusia

Nausea, vomiting, diarrhea, abdominal pain, dizziness, and headache have been reported when SOLOSEC was taken concomitantly with alcohol. [see Dosage and Administration (2.3), Drug Interactions (7.2) and Clinical Pharmacology (12.3)].

Metronidazole, Another Nitroimidazole Agent, Structurally Related to Secnidazole

Cases of severe irreversible hepatotoxicity/acute liver failure, including cases with fatal outcomes with very rapid onset after initiation of systemic use of metronidazole, another nitroimidazole agent structurally related to secnidazole, have been reported in patients with Cockayne syndrome (latency from drug start to signs of liver failure as short as 2 days) [see Contraindications (4)].

7 DRUG INTERACTIONS

7.1 Oral Contraceptives

There was no clinically significant drug interaction between secnidazole and the combination oral contraceptive, ethinyl estradiol plus norethindrone [see Clinical Pharmacology (12.3)]. SOLOSEC can be co-administered with combination oral contraceptives (e.g., ethinyl estradiol plus norethindrone).

7.2 Alcohol

Alcoholic beverages and preparations containing ethanol or propylene glycol should be avoided during SOLOSEC therapy and for 2 days after treatment is stopped.

Nausea, vomiting, diarrhea, abdominal pain, dizziness, and headache have been reported when SOLOSEC was taken concomitantly with alcohol [see Dosage and Administration (2.3), Adverse Reactions (6.2) and Clinical Pharmacology (12.3)].

8 USE IN SPECIFIC POPULATIONS

8.1 Pregnancy

Risk Summary

Limited available data with SOLOSEC use in pregnant women are insufficient to inform a drug associated risk of adverse developmental outcomes. In animal reproduction studies, there were no adverse developmental outcomes when secnidazole was administered orally to pregnant rats and rabbits during organogenesis at doses up to 4 times the clinical dose (see Data).

The estimated background risk of major birth defects and miscarriage for the indicated population is unknown. All pregnancies have a background risk of birth defect, loss, or other adverse outcomes. In the U.S. general population, the estimated background risk of major birth defects and miscarriages in clinically recognized pregnancies is 2 to 4% and 15 to 20%, respectively.

Data

Animal Data

In animal reproduction studies, pregnant rats were dosed orally with secnidazole during organogenesis (gestational days 6-17) at 100, 300 and 1000 mg/kg/day, up to 4 times the clinical dose based on AUC comparisons. Animals showed no evidence of adverse developmental outcomes, but maternal toxicity (including reduced body weight gain) was observed at and above 300 mg/kg/day. In rabbits, no evidence of adverse developmental outcomes was observed when oral doses of secnidazole were administered to dams during organogenesis (gestational days 7-20) at doses up to 100 mg/kg/day (about 0.1 times the clinical dose, based on AUC comparisons). Secnidazole was associated with maternal toxicity (reduced food consumption and markedly reduced body weight gain) in dams at 100 mg/kg/day.

In a peri- and post-natal development study in rats, secnidazole was administered at 30, 100 and 300 mg/kg/day from Day 6 of gestation through Day 20 of lactation. Secnidazole was not associated with any adverse effects on gestation, parturition, lactation or on subsequent development of first generation (F1) and second generation (F2) offspring at these doses, equivalent to up to 1.4 times the clinical dose based on AUC comparisons. Maternal toxicity (reduced gestational body weight gain) was evident at doses of 100 mg/kg and above (about 0.3 times the clinical dose based on AUC comparisons).

8.2 Lactation

Risk Summary

There is no information on the presence of secnidazole in human milk, the effects on the breast-fed child, or the effects on milk production. Other nitroimidazole derivatives are present in human milk. Because of the potential for serious adverse reactions, including tumorigenicity, advise patients that breastfeeding is not recommended during treatment with SOLOSEC and for 96 hours (based on half-life) after administration of SOLOSEC.

Clinical Considerations

A nursing mother may choose to pump and discard her milk during treatment with SOLOSEC and for 96 hours after administration of SOLOSEC and feed her infant stored human milk or formula.

8.4 Pediatric Use

The safety and effectiveness of SOLOSEC for the treatment of bacterial vaginosis have been established in pediatric patients aged 12 to 17 years old. Use of SOLOSEC in this age group is supported by evidence from a multicenter, open-label safety study in 40 pediatric female patients with bacterial vaginosis [see Adverse Reactions (6.1)] and evidence from adequate and well-controlled studies in adult women [see Clinical Studies (14.1)].

The safety and effectiveness of SOLOSEC for the treatment of trichomoniasis have been established in pediatric patients aged 12 to 17 years old. Use of SOLOSEC in this group is based on the extrapolation of clinical trial data from adult women with trichomoniasis, four open-label trials in males with trichomoniasis, and an open-label safety study in pediatric female patients with bacterial vaginosis [see Adverse Reactions (6.1) and Clinical Studies (14.2)].The safety and effectiveness of SOLOSEC in pediatric patients below the age of 12 years have not been established.

8.5 Geriatric Use

Clinical studies with secnidazole did not include sufficient numbers of subjects aged 65 and over to determine whether they respond differently from younger subjects.

11 DESCRIPTION

The active ingredient in SOLOSEC Oral Granules is secnidazole (also named 1-(2-hydroxypropyl)-2-methyl-5-nitroimidazole and 1-(2-methyl-5-nitro-1H-imidazol-1-yl) propan-2-ol), a nitroimidazole antimicrobial.

The molecular formula of secnidazole is C7H11N3O3, the molecular weight is 185.18 and the chemical structure is:

Figure 1: Structure of Secnidazole

Each packet of SOLOSEC contains 4.8 g of off-white to slightly yellowish granules, which contain 2 g of secnidazole and the following inactive ingredients: Eudragit NE30D (ethyl acrylate methyl methacrylate copolymer), polyethylene glycol 4000, povidone, sugar spheres, and talc. Contains no ingredient made from a gluten-containing grain (wheat, barley, or rye).

12 CLINICAL PHARMACOLOGY

12.1 Mechanism of Action

SOLOSEC is a nitroimidazole antimicrobial drug [see Microbiology (12.4)].

12.2 Pharmacodynamics

Secnidazole exposure-response relationships and the time course of pharmacodynamic response are unknown.

Cardiac Electrophysiology

The effect of secnidazole on the QTc interval was evaluated in a Phase 1 randomized, double blind, placebo- and positive-controlled four-period crossover thorough QTc study in 52 healthy adult subjects following single oral granule doses of 2 g and 6 g (3-times the recommended dose). Although there was a positive relationship of the QTc interval with secnidazole concentrations, there was no clinically relevant increase in the QTc interval following either dose.

12.3 Pharmacokinetics

A single oral dose of 2 g of SOLOSEC in healthy adult female subjects, following an overnight fast and admixed with (4 oz) of applesauce, resulted in a mean (SD) secnidazole peak plasma concentration (Cmax) of 45.4 (7.64) mcg/mL and mean (SD) systemic exposure (AUC0-inf) of 1331.6 (230.16) mcg∙hr/mL. Median (range) time to peak concentration (Tmax) was 4.0 (3.0-4.0) hours. Following administration of the 2 g dose, mean secnidazole plasma concentrations decreased to 22.1 mcg/mL at 24 hours, 9.2 mcg/mL at 48 hours, 3.8 mcg/mL at 72 hours, and 1.4 mcg/mL at 96 hours.

Absorption

Effect of Food

Administration of 2 g of SOLOSEC admixed with applesauce followed by ingestion of a high-fat meal (approximately 150 protein calories, 250 carbohydrate calories, and 500-600 fat calories) resulted in no significant change in the rate (Cmax) and extent (AUC) of secnidazole exposure as compared to administration when admixed with applesauce and taken under fasted conditions. There was no effect of admixing SOLOSEC with pudding and yogurt as compared to admixing with applesauce (Table 2). [see Dosage and Administration (2.2)]

Table 2: Pharmacokinetic Parameters Following Single Dose Administration of SOLOSEC 2 g Given Orally
 |  | Cmax (mcg/mL) | Tmax (hr) [Median (range)] | AUC (mcg*hr/mL)
Fasted [Admixed with applesauce] (N=23) | Mean (SD) | 41.2 (5.5) | 4.0 (3.0 – 6.0) | 1261.5 (236.5)
Fasted [Admixed with applesauce] (N=23) | Range | 32.7 – 56.2 |  | 874.3 – 1750.4
High fat meal (N=23) | Mean (SD) | 40.1 (4.9) | 6.0 (4.0 – 8.0) | 1248.2 (291.6)
High fat meal (N=23) | Range | 31.0 – 47.7 |  | 762.0 – 1769.4
Mixed with applesauce (N=24) | Mean (SD) | 44.1 (4.6) | 4.0 (3.0 – 6.1) | 1523 (372.2)
Mixed with applesauce (N=24) | Range | 37.4 – 55.6 |  | 1040 – 2350
Mixed with pudding (N=23) | Mean (SD) | 45.6 (5.1) | 4.0 (4.0 – 6.0) | 1447 (331.0)
Mixed with pudding (N=23) | Range | 38.6 – 60.4 |  | 997 – 2130
Mixed with yogurt (N=24) | Mean (SD) | 43.4 (5.4) | 4.0 (4.0 – 8.0) | 1478 (335.0)
Mixed with yogurt (N=24) | Range | 36.3 – 59.3 |  | 965 – 2240

Distribution

The apparent volume of distribution of secnidazole is approximately 42 L. The plasma protein binding of secnidazole is <5%.

Elimination

The total body clearance of secnidazole is approximately 25 mL/min. The renal clearance of secnidazole is approximately 3.9 mL/min.

The plasma elimination half-life for secnidazole is approximately 17 hours.

Metabolism

Secnidazole is metabolized in vitro via oxidation by human hepatic CYP450 enzyme system with ≤ 1% conversion to metabolites.

Excretion

Approximately 15% of a 2 g oral dose of SOLOSEC is excreted as unchanged secnidazole in the urine.

Drug Interaction Studies

Oral Contraceptives

Concomitant administration of 2 g of SOLOSEC with the combination oral contraceptive (OC), ethinyl estradiol (EE) plus norethindrone (NE), to healthy adult female subjects resulted in a decrease in mean Cmax of EE of 29%, and no significant effect on the mean AUC of EE. Administration of 2 g of SOLOSEC 1 day before combination OC administration resulted in no significant effect on mean Cmax or AUC of EE.

Concomitant administration of 2 g of SOLOSEC with the combination OC resulted in no significant effect on mean Cmax and AUC of NE (increases of 13% and 16%, respectively). Administration of 2 g of SOLOSEC 1 day before combination OC administration also resulted in no significant effect on mean Cmax and AUC of NE. [see Drug Interactions (7.1)]

Ethanol Metabolism

In vitro studies showed that secnidazole had no effect on aldehyde dehydrogenase activity. However, postmarketing observations of adverse reactions of nausea, vomiting, diarrhea, abdominal pain, dizziness, and headache with concomitant use of SOLOSEC and alcohol have been reported [see, Dosage and Administration (2.3), Adverse Reactions (6.2), and Drug Interactions (7.2)].

12.4 MICROBIOLOGY

Mechanism of Action

Secnidazole, like other 5-nitroimidazoles, enters the bacterial and Trichomonas cells where the nitro group is reduced by nitroreductase enzyme(s) leading to the production of radical anions and a series of intermediates, depletion of thiols, DNA damage, and death of susceptible isolates of Gram positive bacteria, Gram negative bacteria and T. vaginalis.

Resistance

The potential for development of resistance to secnidazole by bacteria and T. vaginalis associated with bacterial vaginosis and trichomoniasis, respectively, was not examined. The mechanism of resistance, like for other nitroimidazoles, appears to be multifactorial that include decreased uptake of the drug, higher efflux activity, and/or altered nitroreductase activity.

Bacterial and T. vaginalis isolates exhibiting reduced in vitro susceptibility to metronidazole also show reduced susceptibility to secnidazole. The clinical significance of such an effect is unknown.

Antibacterial Activity

Culture and sensitivity testing of bacteria are not routinely performed to establish the diagnosis of bacterial vaginosis [see Indications and Usage (1.1)]; standard methodology for the susceptibility testing of potential bacterial pathogens, Gardnerella vaginalis or Mobiluncus spp. has not been defined.

The following in vitro data are available, but their clinical significance is unknown. Secnidazole is active in vitro against most isolates of the following organisms reported to be associated with bacterial vaginosis:

Bacteroides spp.

Gardnerella vaginalis

Prevotella spp.

Mobiluncus spp.

Megasphaera-like type I/II

Anti-protozoal Activity

Trichomonas vaginalis

Standardized susceptibility tests do not exist for use in clinical microbiology laboratories.

13 NONCLINICAL TOXICOLOGY

13.1 Carcinogenesis, Mutagenesis, Impairment of Fertility

Carcinogenesis

Nitroimidazoles, which have similar chemical structures to secnidazole, have been associated with tumors affecting the liver, lungs, mammary, and lymphatic tissues in animals after lifetime exposures. It is unclear if these positive tumor findings in lifetime rodent studies of these nitroimidazoles indicate a risk to patients taking a single dose of secnidazole to treat bacterial vaginosis or trichomoniasis.

Mutagenesis

Secnidazole was positive in the Bacterial Reverse Mutation Assay but was negative for the rat micronucleus test and mouse lymphoma test.

Impairment of Fertility

In a rat fertility study, females were dosed for two weeks prior to mating until Day 7 of gestation with males that were dosed for a minimum of 28 days before cohabitation. No parental toxicity or adverse effects on mating performance, estrous cycles, fertility or conception was observed at doses of up to the maximum tolerated dose (300 mg/kg/day, approximately 1.4 times the recommended dose based on AUC comparisons).

14 CLINICAL STUDIES

14.1 Bacterial Vaginosis

Two randomized placebo-controlled clinical trials (Trial 1 and Trial 2) with similar designs were conducted to evaluate the efficacy of SOLOSEC 2 gram for the treatment of bacterial vaginosis. A diagnosis of bacterial vaginosis was defined as all of (a) the presence of an off-white (milky or gray), thin, homogeneous vaginal discharge; (b) a vaginal pH ≥ 4.7; (c) the presence of Clue cells ≥ 20% of the total epithelial cells on a microscopic examination of the vaginal saline wet mount; (d) a positive "whiff" test (detection of amine odor on addition of 10% KOH solution to a sample of the vaginal discharge); and (e) a Nugent score ≥ 4.

Trial 1 enrolled 144 non-pregnant female patients aged 19 to 54 years and Trial 2 enrolled 189 non-pregnant females aged 18 to 54 years. Black or African American subjects in both trials were 54%. Efficacy was assessed by clinical outcome evaluated 21 to 30 days following a single dose of SOLOSEC. A clinical responder was defined as "normal" vaginal discharge, negative "whiff" test, and clue cells <20%. Additional endpoints included Nugent score cure (Nugent score of 0-3) and therapeutic outcome. A therapeutic responder was defined as a clinical responder with a Nugent score cure. In Trial 2, the endpoints were also assessed at Day 7-14.

In both trials, a statistically significantly greater percentage of patients experienced clinical response, Nugent score cure, and therapeutic response at 21 to 30 days following a single dose of SOLOSEC compared to placebo. Statistically significant results for the endpoints were also achieved at Day 7-14 in Trial 2.

The percentage of patients with clinical response was also consistently higher in both trials in the SOLOSEC arm compared to placebo among all subsets of patients: number of prior episodes of bacterial vaginosis (≤ 3 episodes and ≥ 4 episodes) in past 12 months, baseline Nugent score (score 4-6 and score 7-10), and race (Black/African American and White). Tables 3 and 4 describe the efficacy of SOLOSEC in the treatment of bacterial vaginosis.

Table 3. Efficacy of SOLOSEC for Treatment of Bacterial Vaginosis in Two Randomized, Double-Blind, Placebo-Controlled Trials in Modified-Intent-to-Treat Population at 21-30 Days
 | Trial 1 |  | Trial 2
 | SOLOSEC (N=62) [N=number of patients in treatment group (modified intent-to-treat population defined as all patients randomized who had a baseline Nugent score ≥4 and were negative for other sexually transmitted infections at baseline).] n (%) | Placebo (N=62) n (%) | SOLOSEC (N=107) n (%) | Placebo (N=57) n (%)
Clinical Responder [Patients missing one or more of the clinical assessments were considered as non-responders/not cured.] | 42 (67.7) | 11 (17.7) | 57 (53.3) | 11 (19.3)
Clinical Responder [Patients missing one or more of the clinical assessments were considered as non-responders/not cured.] | 50.0 (33.4, 66.7) [Difference in response (SOLOSEC – placebo) and 95% confidence interval] |  | 34.0 (18.7, 49.3)
Clinical Responder [Patients missing one or more of the clinical assessments were considered as non-responders/not cured.] | p<0.001 |  | p<0.001
Nugent Score Cure [Patients with missing Nugent scores were considered Nugent score failures.] | 25 (40.3) | 4 (6.5) | 47 (43.9) | 3 (5.3)
Nugent Score Cure [Patients with missing Nugent scores were considered Nugent score failures.] | 33.8 (18.5, 49.1) |  | 38.6 (26.2, 51.0)
Nugent Score Cure [Patients with missing Nugent scores were considered Nugent score failures.] | p<0.001 |  | p<0.001
Therapeutic Responder | 25 (40.3) | 4 (6.5) | 37 (34.6) | 2 (3.5)
Therapeutic Responder | 33.8 (18.5, 49.1) |  | 31.1 (19.6, 42.6)
Therapeutic Responder | p<0.001 |  | p<0.001

Table 4. Efficacy of SOLOSEC for Treatment of Bacterial Vaginosis in Trial 2 in Modified-Intent-to-Treat Population at 7-14 Days
 | Trial 2
 | SOLOSEC (N=107) [N=number of patients in treatment group (modified intent-to-treat population defined as all patients randomized who had a baseline Nugent score ≥4 and were negative for other sexually transmitted infections at baseline).] n (%) | Placebo (N=57) n (%)
Clinical Responder [Patients missing one or more of the clinical assessments were considered as non-responders/not cured.] | 62 (57.9) | 14 (24.6)
Clinical Responder [Patients missing one or more of the clinical assessments were considered as non-responders/not cured.] | 33.3 (17.4, 49.2) [Difference in response (SOLOSEC – placebo) and 95% confidence interval]
Clinical Responder [Patients missing one or more of the clinical assessments were considered as non-responders/not cured.] | p<0.001
Nugent Score Cure [Patients with missing Nugent scores were considered Nugent score failures.] | 49 (45.8) | 2 (3.5)
Nugent Score Cure [Patients with missing Nugent scores were considered Nugent score failures.] | 42.3 (30.4, 54.2)
Nugent Score Cure [Patients with missing Nugent scores were considered Nugent score failures.] | p<0.001
Therapeutic Responder | 37 (34.6) | 2 (3.5)
Therapeutic Responder | 31.1 (19.6, 42.6)
Therapeutic Responder | p<0.001

14.2 Trichomoniasis

The efficacy of a single 2-gram oral dose of SOLOSEC for the treatment of trichomoniasis was evaluated in a multi-center, prospective, randomized, placebo-controlled, delayed treatment, double-blind, trial (Trial 5, NCT03935217). A total of 147 female patients from the United States aged 15 to 65 years were enrolled and randomized 1:1 to receive either SOLOSEC or placebo. The modified intent-to-treat (mITT) population included all randomized patients who were culture positive for T. vaginalis and negative for other sexually transmitted infections. Of the 131 female patients in the mITT population, the median age was 36 years, and 90.8% were African American. Baseline clinical symptoms of vaginal itching, discharge, or odor were reported in 111 (84.7%) patients. Following initial dosing, the test of cure (TOC) visit occurred 6 to 12 days later. At the TOC visit, patients received the opposite treatment (placebo patients received SOLOSEC and vice versa) with a return visit 7 to 12 days later.

Results for microbiological cure, defined as testing negative for T. vaginalis, for the mITT population are presented in Table 5. The microbiological cure rate at the TOC visit was significantly higher in the SOLOSEC treatment group compared to the placebo group.

Table 5: Microbiological Cure Rate in Trichomoniasis Patients at TOC Visit (mITT Population) in Trial 5
Endpoint | SOLOSEC 2 g n/N (%) [N: number of patients in treatment group. For microbiological cure, included all subjects in the modified intent-to-treat (mITT) population, defined as all randomized patients who were culture positive for Trichomonas vaginalis and negative for other sexually transmitted infections.] | Placebo n/N (%), [n placebo subjects with positive T. vaginalis culture at TOC, receiving delayed SOLOSEC treatment showed a comparable microbiological cure rate 7-12 days later (56/63 (88.9%), 95% CI: 78.4%, 95.4%) to the 92.2% cure rate for the initially SOLOSEC treated subjects.] | Treatment Difference (95% CI)
Microbiological Cure [InPouch™ TV test negative for T. vaginalis.] , [Subjects with no test results are assumed to be positive (1 SOLOSEC and 3 placebo subjects).] | 59/64 (92.2) | 1/67 (1.5) | 90.7 (80.7, 96.5) [Exact CI from the Score Method.] , [P-value <0.001 versus placebo from a CMH test adjusted for clinical symptoms (present/absent) of trichomoniasis at baseline.]
CI = confidence interval; TOC = Test of Cure

The single oral 2 g secnidazole dose was also assessed in four open-label trials in males (one comparative study with metronidazole and ornidazole in males only^1 and three single-arm studies in males and females^2,3,4). Parasitological evaluation was performed both pre- and post-treatment and reported cure rates ranged from 91.7% (165/180) to 100% (30/30) at time points ranging from 2 to 20 days (n=437, 211 males and 226 females). In addition, the natural history of trichomoniasis in men was evaluated in one study.^5 The spontaneous resolution during a mean follow-up of 16 ± 12 days was noted in 36% (5/14) (95% CI: 12.8%, 64.9%) of untreated men.

15 REFERENCES

1. Özbilgin A, Özbel Y, Alkan MZ et al. Trichomoniasis in non-gonococcic urethritis among male patients. J Egypt Soc Parasitol. 1994; 24(3):621-625.
2. Dyudyun AD, Polyon NM, Gorbuntsov VV. Secnidazole in complex treatment of patients with urogenital trichomoniasis. Dermatovenerology Cosmetology Sexopathology. 2016;1(4): 287-292.
3. Siboulet A, Catalan F, Videau D, Niel G. Urogenital trichomoniasis. Trials with a long half-life imidazole: secnidazole. Med Mal Infect. 1977;7(9):400-409.
4. Videau D, Niel G, Siboulet A, Catalan F. Secnidazole: A 5-nitroimidazole derivative with a long half-life. Br J Vener Dis. 1978;54(2):77-80.
5. Krieger JN, Verdon M, Siegel N, Holmes KK. Natural history of urogenital trichomoniasis in men. J Urol. 1993 Jun;149(6):1455-8.

16 HOW SUPPLIED / STORAGE AND HANDLING

SOLOSEC (secnidazole) Oral Granules, 2 g, consists of off-white to slightly yellowish granules containing secnidazole. SOLOSEC is supplied in one unit-of-use child-resistant foil packet of granules in an individual carton. Each packet contains 4.8 g of granules containing 2 g secnidazole. SOLOSEC is supplied as follows:

NDC 69751-400-01 carton containing one unit-of-use child-resistant 2 g foil packet.

STORAGE AND HANDLING

Store at 20°C to 25°C (68°F to 77°F); excursions permitted to 15°C to 30°C (59°F to 86°F) [See USP Controlled Room temperature].

17 PATIENT COUNSELING INFORMATION

Advise the patient to read the FDA-approved patient labeling (Patient Information and Instructions for Use).

Administration Instructions

Instruct the patient:

- To sprinkle the entire contents of the packet of SOLOSEC onto applesauce, yogurt or pudding and take all the mixture within 30 minutes without chewing or crunching the granules.
- That after consuming the mixture, they may take a glass of water to aid in swallowing.
- That SOLOSEC is not intended to be dissolved in any liquid.

Advise the patient that SOLOSEC may be taken without regard to the timing of meals.

Vulvovaginal Candidiasis

Advise the patient that use of SOLOSEC may result in vulvovaginal candidiasis that may require treatment with an antifungal agent. [see Warnings and Precautions (5.1)]

Alcohol

Advise patients to avoid consumption of alcoholic beverages and preparations containing ethanol or propylene glycol during SOLOSEC therapy and for 2 days afterward because nausea, vomiting, diarrhea, abdominal pain, dizziness, and headache may occur [see Dosage and Administration (2.3), Adverse Reactions (6.2), Drug Interactions (7.2), and Clinical Pharmacology (12.3)].

Lactation

Advise women not to breastfeed during treatment with SOLOSEC and to discontinue breastfeeding for 96 hours following the administration of SOLOSEC. Also, advise a nursing mother that she may choose to pump and discard her milk for 96 hours after administration of SOLOSEC and feed her infant stored human milk or formula [see Use in Specific Populations (8.2)].

Drug Resistance

Patients should be counseled that antibacterial drugs including SOLOSEC should only be used to treat bacterial infections. They do not treat viral infections (e.g., the common cold). When SOLOSEC is prescribed to treat a bacterial infection, patients should be told that although it is common to feel better early in the course of therapy, the medication should be taken exactly as directed. Skipping doses or not completing the full course of therapy may (1) decrease the effectiveness of the immediate treatment and (2) increase the likelihood that bacteria will develop resistance and will not be treatable by SOLOSEC or other antibacterial drugs in the future.

Manufactured for Evofem, Inc., a wholly owned subsidiary of Evofem Biosciences, Inc.
San Diego, CA 92130

© 2024 Evofem, Inc. All rights reserved.

PN-5055 R02

PATIENT INFORMATION
SOLOSEC®
(SO-lo-sec)
(secnidazole) oral granules

What is SOLOSEC?
SOLOSEC is a prescription medicine used to treat:

- bacterial vaginal infections in females 12 years of age and older.
- trichomoniasis, a common sexually transmitted infection (STI), in people 12 years of age and older. Sexual partners should be treated at the same time. People should avoid having sex until they and their sex partners are treated (for example, when therapy has been completed and any symptoms have resolved) to help prevent reinfection.

It is not known if SOLOSEC is safe and effective in children under 12 years of age.

Do not take SOLOSEC if you:

- are allergic to secnidazole or other nitroimidazole medicines.
- have Cockayne syndrome.

Before taking SOLOSEC, tell your healthcare provider about all of your medical conditions, including if you:

- are pregnant or plan to become pregnant. It is not known if SOLOSEC will harm your unborn baby. Tell your healthcare provider if you become pregnant during treatment with SOLOSEC.
- are breastfeeding or plan to breastfeed. You should not breastfeed for 96 hours (4 days) after taking SOLOSEC. SOLOSEC may pass into breast milk. Talk with your healthcare provider about the best way to feed your baby while taking SOLOSEC.

Tell your healthcare provider about all the medicines you take, including prescription and over-the-counter medicines, vitamins, and herbal supplements.

How should I take SOLOSEC?

- See the Instructions for Use at the end of this Patient Information leaflet for instructions on how to take SOLOSEC.
- Take SOLOSEC exactly as your healthcare provider tells you to. Do not take SOLOSEC more often than it is prescribed.

What should I avoid while taking SOLOSEC?
Avoid drinking alcohol during treatment with SOLOSEC and for 2 days (48 hours) after you take SOLOSEC because the following side effects may happen:

- nausea
- vomiting

- diarrhea
- stomach (abdominal) pain

- dizziness
- headache

What are the possible side effects of SOLOSEC?
SOLOSEC can cause side effects including vaginal yeast infections. Symptoms of a vaginal yeast infection include white or yellowish discharge (discharge may be lumpy or look like cottage cheese) and vaginal itching.
The most common side effects of SOLOSEC include headache, nausea, vomiting, diarrhea, abdominal pain, vaginal itching and a bad, bitter or metallic taste in your mouth (dysgeusia).
These are not all of the possible side effects of SOLOSEC. Call your doctor for medical advice about side effects. You may report side effects to FDA at 1-800-FDA-1088.

General information about the safe and effective use of SOLOSEC.
Medicines are sometimes prescribed for purposes other than those listed in a Patient Information leaflet. Do not use SOLOSEC for a condition for which it was not prescribed. Do not give SOLOSEC to other people, even if they have the same symptoms that you have. It may harm them. You can ask your pharmacist or healthcare provider for information about SOLOSEC that is written for health professionals.

What are the ingredients in SOLOSEC?
Active ingredient: secnidazole
Inactive ingredients: Eudragit NE30D (ethyl acrylate methyl methacrylate copolymer), polyethylene glycol 4000, povidone, sugar spheres, and talc.
Contains no ingredient made from a gluten-containing grain (wheat, barley, or rye).
For more information, visit www.solosec.com or contact Evofem at 1-833-EVFMBIO (1-833-383-6246).

INSTRUCTIONS FOR USE

SOLOSEC®

(SO-lo-sec)
(secnidazole) oral granules

For oral use (by mouth) only.

How to take SOLOSEC?

1. Open the SOLOSEC packet by folding over the corner marked by an arrow (see diagram) and tearing across the top.
2. Sprinkle the entire contents of the SOLOSEC packet onto applesauce, yogurt or pudding. The granules will not dissolve. Take within 30 minutes without chewing or crunching the granules.
3. You can drink a glass of water after taking SOLOSEC to help with swallowing.
4. You should not try to dissolve the medicine in water or any other liquid.

Important Information

- SOLOSEC may be taken before, after or during a meal.
- Take 1 entire packet of SOLOSEC at one time. Do not take only part of the medicine and save a portion for later.
- Avoid drinking alcohol during treatment with SOLOSEC and for 2 days (48 hours) after you take SOLOSEC.

How should I store SOLOSEC?

- Store SOLOSEC at room temperature between 68°F to 77°F (20°C to 25°C).
- Keep SOLOSEC and all medicines out of the reach of children.

This Patient Information and Instructions for Use have been approved by the US Food and Drug Administration. Issued: 10/2024

Manufactured for Evofem, Inc., a wholly owned subsidiary of Evofem Biosciences, Inc.

San Diego, CA 92130

© 2024 Evofem, Inc. All Rights Reserved.

PN-5055 R02

PRINCIPAL DISPLAY PANEL - 2 g Packet Carton

NDC 69751-400-01

Rx Only

solosec® 2g
secnidazole

Oral Granules

1 Unit-of-Use Packet

EVOFEM
BIOSCIENCES®